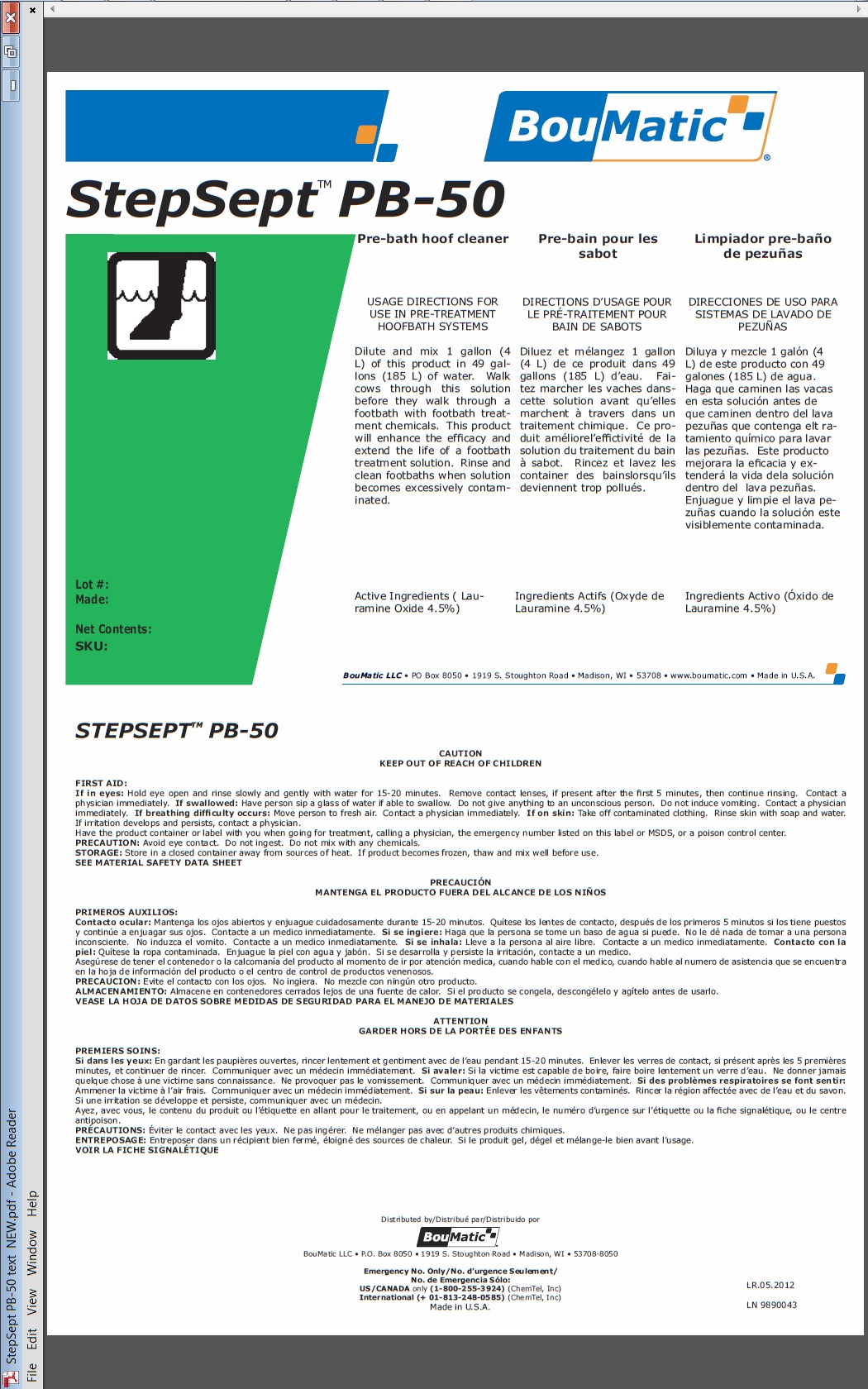 DRUG LABEL: StepSept PB-50
NDC: 48106-1151 | Form: LIQUID
Manufacturer: BouMatic, LLC
Category: animal | Type: OTC ANIMAL DRUG LABEL
Date: 20120101

ACTIVE INGREDIENTS: LAURAMINE OXIDE 450 mL/10 L

StepSept PB-50

INDICATIONS AND USAGE

Pre-bath hoof cleaner
USAGE DIRECTIONS FOR USE IN PRE-TREATMENT HOOFBATH SYSTEMS
Dilute and mix 1 gallon (4 L) of this product in 49 gallons (185 L) of water. Walk cows through this solution before they walk through a footbath with footbath treatment chemicals. This product will enhance the efficacy and extend the life of a footbath treatment solution. Rinse and clean footbaths when solution becomes excessively contaminated.
Active Ingredients (Lauramine
Oxide 4.5%)

PRECAUTIONS

CAUTION
KEEP OUT OF REACH OF CHILDREN
FIRST AID:
If in eyes: Hold eye open and rinse slowly and gently with water for 15-20 minutes. Remove contact lenses, if present after the first 5 minutes, then continue rinsing. Contact a physician immediately. If swallowed: Have person sip a glass of water if able to swallow. Do not give anything to an unconscious person. Do not induce vomiting. Contact a physician immediately. If breathing difficulty occurs: Move person to fresh air. Contact a physician immediately.
If on skin: Take off contaminated clothing. Rinse skin with soap and water. If irritation develops and persists, contact a physician.
Have the product container or label with you when going for treatment, calling a physician, the emergency number listed on this label or MSDS, or a poison control center.
PRECAUTION: Avoid eye contact. Do not ingest. Do not mix with any chemicals.
STORAGE: Store in a closed container away from sources of heat. If product becomes frozen, thaw and mix well before use.
SEE MATERIAL SAFETY DATA SHEET